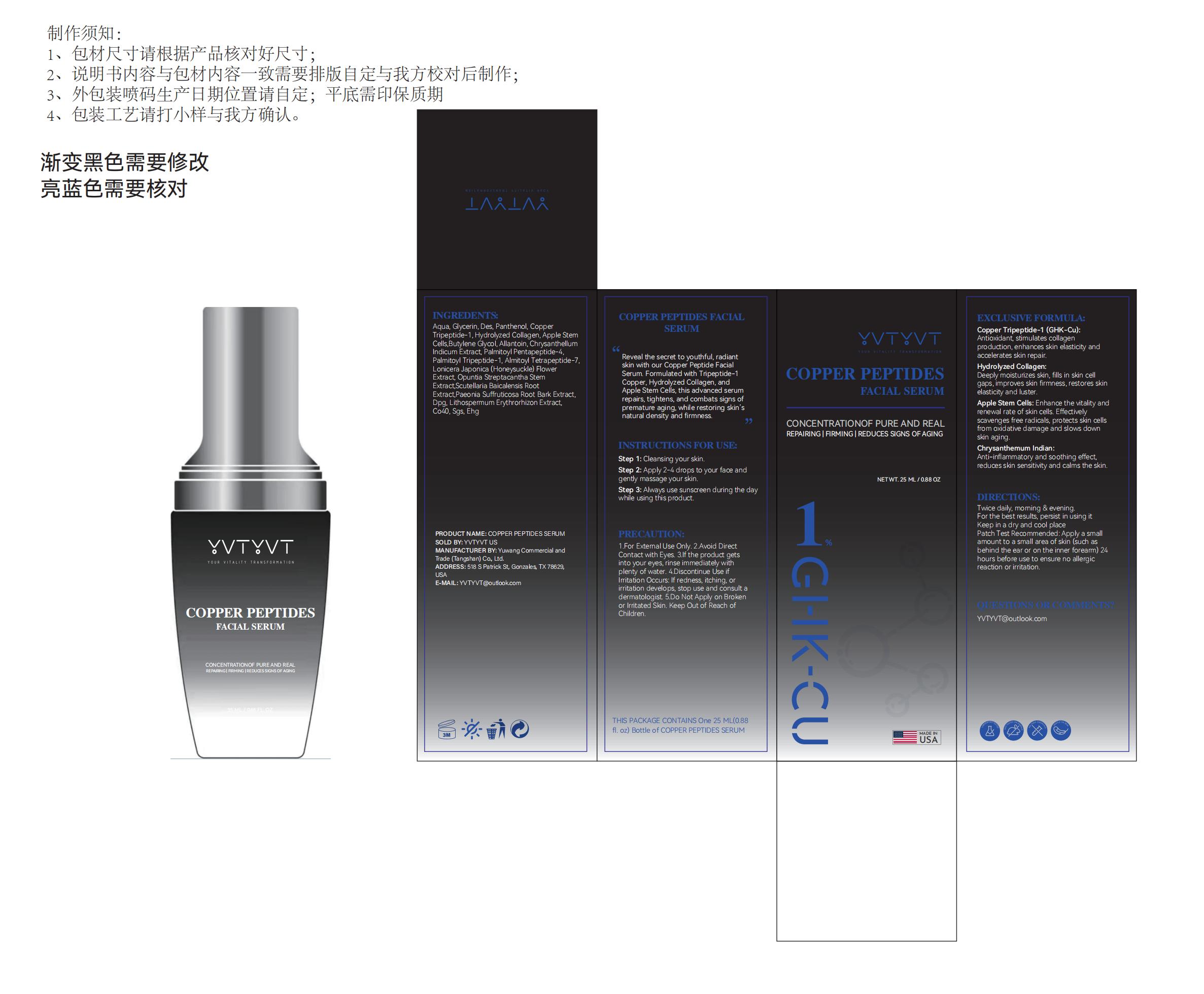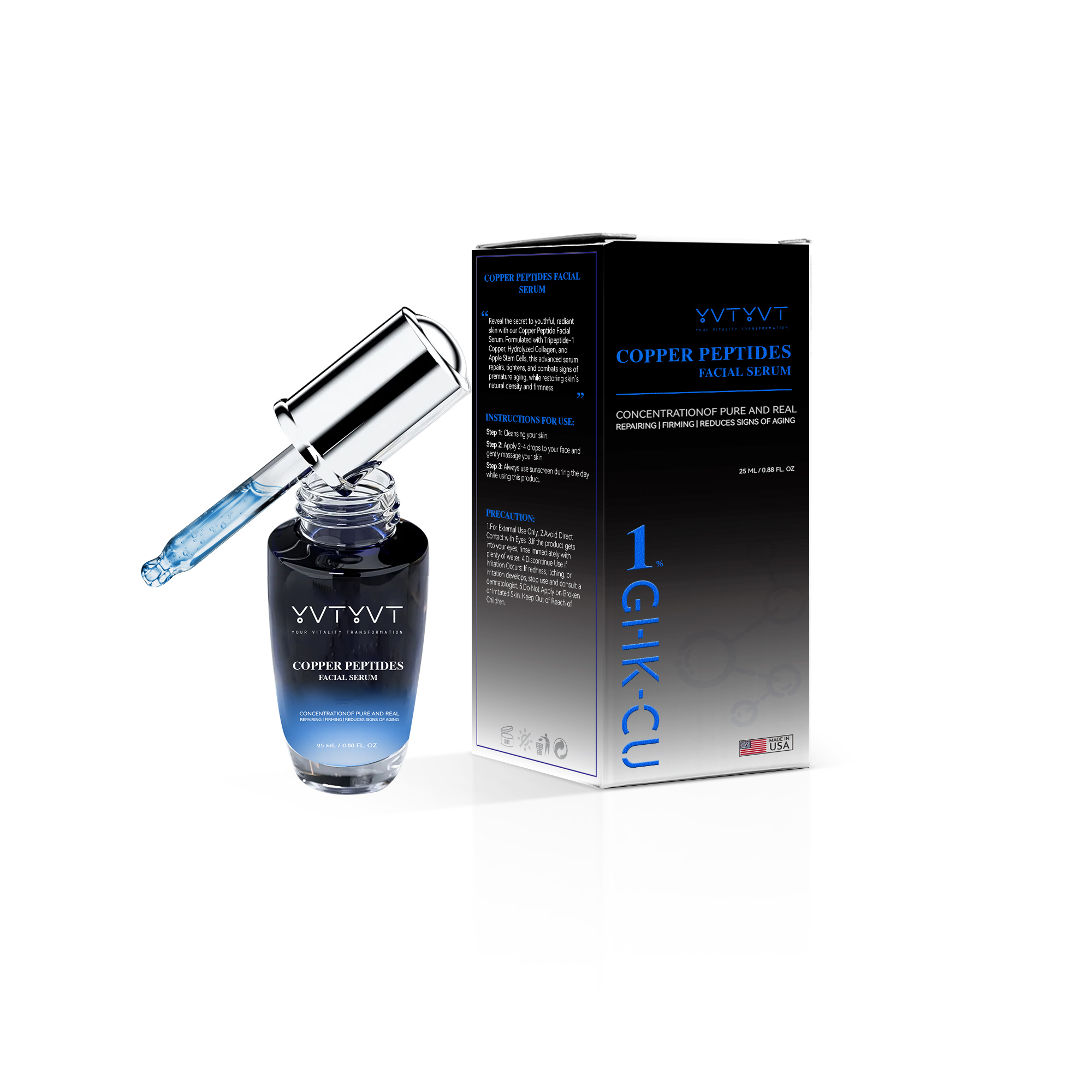 DRUG LABEL: YVTYVT Copper Peptides Face Serum
NDC: 85212-0029 | Form: CREAM
Manufacturer: Beijing JUNGE Technology Co., Ltd.
Category: otc | Type: HUMAN OTC DRUG LABEL
Date: 20250316

ACTIVE INGREDIENTS: COPPER TRIPEPTIDE-1 1 g/100 mL
INACTIVE INGREDIENTS: AQUA 74 mL/100 mL; PALMITOYL PENTAPEPTIDE-4 0.2 mL/100 mL; PALMITOYL TETRAPEPTIDE-7 0.2 mL/100 mL; GLYCERIN 5 mL/100 mL; DIPOTASSIUM GLYCYRRHIZATE 0.1 mL/100 mL; SODIUM POLYGLUTAMATE (200000 MW) 0.2 mL/100 mL; GLYCERYL ACRYLATE/ACRYLIC ACID COPOLYMER (300000 CP AT 2%) 0.1 mL/100 mL; HYDROXYACETOPHENONE 0.5 mL/100 mL; BUTYLENE GLYCOL 0.5 mL/100 mL; OPUNTIA STREPTACANTHA STEM 0.2 mL/100 mL; PEG-40 HYDROGENATED CASTOR OIL 0.1 mL/100 mL; DIETHOXYETHYL SUCCINATE 2 mL/100 mL; PANTHENOL 2 mL/100 mL; ETHYLHEXYLGLYCERIN 0.1 mL/100 mL; CHRYSANTHELLUM INDICUM FLOWER OIL 0.5 mL/100 mL; PALMITOYL TRIPEPTIDE-1 0.2 mL/100 mL; LONICERA JAPONICA FLOWER 0.2 mL/100 mL; SCUTELLARIA BAICALENSIS ROOT 0.1 mL/100 mL; SODIUM GUAIAZULENE SULFONATE 0.1 mL/100 mL; BETAINE 5 mL/100 mL; AMMONIUM ACRYLOYLDIMETHYLTAURATE/VP COPOLYMER 0.5 mL/100 mL; ERYTHRITOL 5 mL/100 mL; HYDROLYZED SERICIN (ENZYMATIC; 20000 MW) 1 mL/100 mL; 1,2-HEXANEDIOL 0.5 mL/100 mL; ALLANTOIN 0.5 mL/100 mL; PAEONIA SUFFRUTICOSA ROOT BARK 0.1 mL/100 mL; LITHOSPERMUM ERYTHRORHIZON ROOT 0.1 mL/100 mL

INSTRUCTIONS FOR USE

Step 1: Cleansing your skin.
Step 2: Apply 2-4 drops to your face and gently massage your skin.
Step 3: Always use sunscreen during the day while using this product.

GENERAL PRECAUTIONS

1.For External Use Only.

2.Avoid Direct Contact with Eyes.

3.If the product gets into your eyes, rinse immediately with plenty of water.

4.Discontinue Use if Irritation Occurs: If redness, itching, or irritation develops, stop use and consult a dermatologist.

5.Do Not Apply on Broken or Irritated Skin. Keep Out of Reach of Children.

QUESTIONS

YVTYVT@outlook.com

yuwangshangmao(tangshan)youxiangongsi

DOSAGE AND ADMINISTRATION

Twice daily, morning & evening.
For the best results, persist in using it
Keep in a dry and cool place
Patch Test Recommended: Apply a small
amount to a small area of skin (such as
behind the ear or on the inner forearm) 24
hours before use to ensure no allergic
reaction or irritation.

BOXED WARNING

For external use only. Keep out of reach of children.Avoid contact with eyes.

Keep out of reach of children. If swallowed, get medical help or contact a Poison Control Center right away.

INDICATIONS AND USAGE

It repairs, tightens, and combats signs of premature aging, while restoring skin’s natural density and firmness.

Twice daily, morning & evening.
For the best results, persist in using it

PURPOSE

CONCENTRATIONOF PURE AND REAL
REPAIRING | FIRMING | REDUCES SIGNS OF AGING

INACTIVE INGREDIENT

AQUA
GLYCERIN
ERYTHRITOL
DIETHOXYETHYL SUCCINATE
PANTHENOL

HYDROLYZED PORCINE COLLAGEN (ENZYMATIC; 3000 MW)

1,2-HEXANEDIOL
HYDROXYACETOPHENONE
AMMONIUM ACRYLOYLDIMETHYLTAURATE/VP COPOLYMER
BUTYLENE GLYCOL
PALMITOYL PENTAPEPTIDE-4
PALMITOYL TRIPEPTIDE-1
PALMITOYL TETRAPEPTIDE-7

LONICERA JAPONICA (HONEYSUCKLE) FLOWER EXTRACT
OPUNTIA STREPTACANTHA STEM EXTRACT
SCUTELLARIA BAICALENSIS ROOT EXTRACT
PAEONIA SUFFRUTICOSA ROOT BARK EXTRACT
DIPOTASSIUM GLYCYRRHIZATE
SODIUM POLYGLUTAMATE
LITHOSPERMUM ERYTHRORHIZON EXTRACT
PEG-40 HYDROGENATED CASTOR OIL
SODIUM GUAIAZULENE SULFONATE
ETHYLHEXYLGLYCERIN
MALUS DOMESTICA

WARNINGS

For external use only. Keep out of reach of children.Avoid contact with eyes.